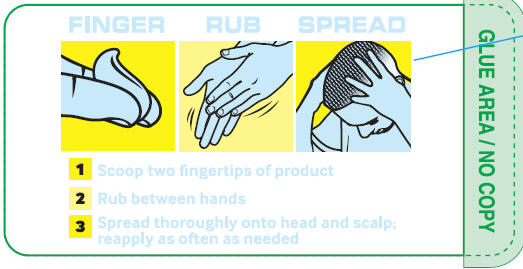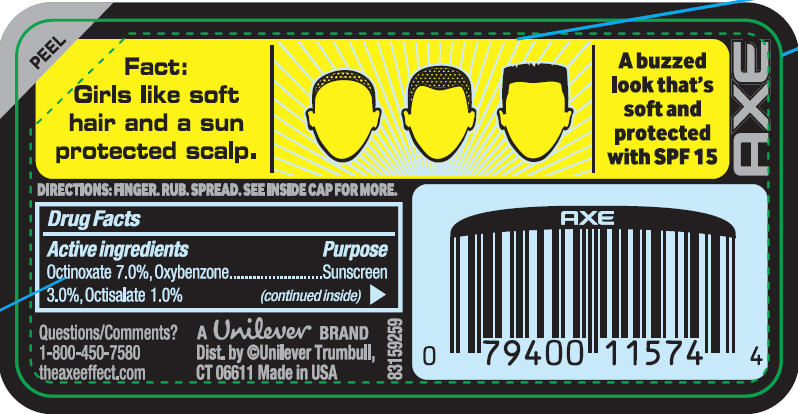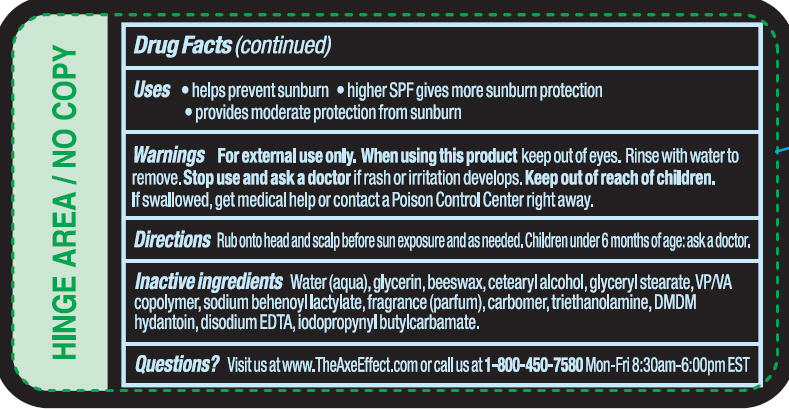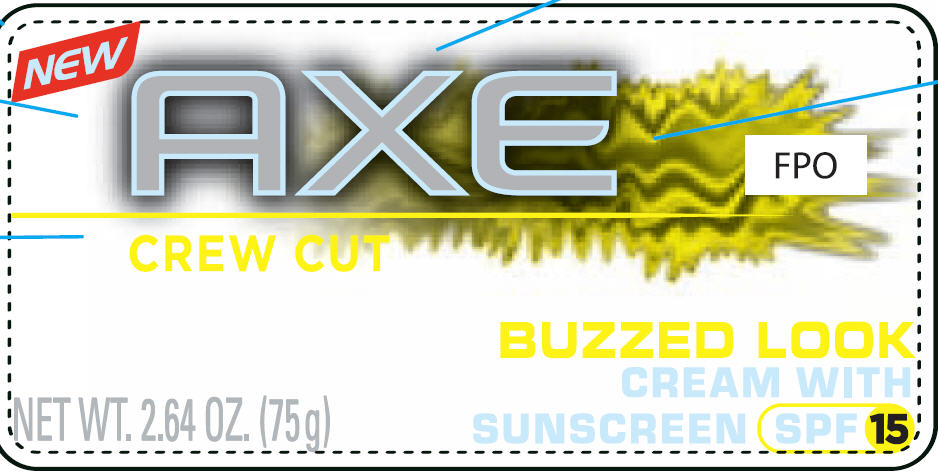 DRUG LABEL: Axe Crew Cut
NDC: 64942-1161 | Form: CREAM
Manufacturer: CONOPCO Inc. d/b/a Unilever
Category: otc | Type: HUMAN OTC DRUG LABEL
Date: 20110329

ACTIVE INGREDIENTS: OCTINOXATE 7.0 g/100 g; OXYBENZONE 3.0 g/100 g; OCTISALATE 1.0 g/100 g
INACTIVE INGREDIENTS: WATER; GLYCERIN; WHITE WAX; CETOSTEARYL ALCOHOL; GLYCERYL MONOSTEARATE; TROLAMINE; DMDM HYDANTOIN; EDETATE DISODIUM; IODOPROPYNYL BUTYLCARBAMATE; CARBOMER HOMOPOLYMER TYPE C

Axe Crew Cut Buzzed Look Cream with Sunscreen SPF 15

Active ingredients
Octinoxate 7.0%, Oxybenzone 3.0%, Octisalate 1.0%

Purpose
Sunscreen

Uses
helps prevent sunburn
higher SPF gives more sunburn protection
provides moderate protection from sunburn

Warnings
For external use only.
If swallowed, get medical help or contact a Poison Control Center right away.

When using this product keep out of eyes. Rinse with water to remove.

Stop use and ask a doctor if rash or irritation develops.

Keep out of reach of children.

Directions
Rub onto head and scalp before sun exposure and as needed. Children under 6 months of age: ask a doctor.

Inactive ingredients
Water, Glycerin, Beeswax, Cetearyl Alcohol, Glyceryl Stearate, VP/VA Copolymer, Sodium Behenoyl Lactylate, Fragrance, Carbomer, Triethanolamine, DMDM Hydantoin, Disodium EDTA, Iodopropynyl Butylcarbamate.

Questions?
Visit us at www.TheAxeEffect.com or call us at 1-800-450-7580 Mon-Fri 8:30am - 6:00pm EST

PACKAGE LABEL

Axe Buzzed Cut PDP front

PACKAGE LABEL

Axe Buzz SPF15 back 1

PACKAGE LABEL

Axe Buzz SPF15 back 2

PACKAGE LABEL

Axe Buzz SPF15 back 3